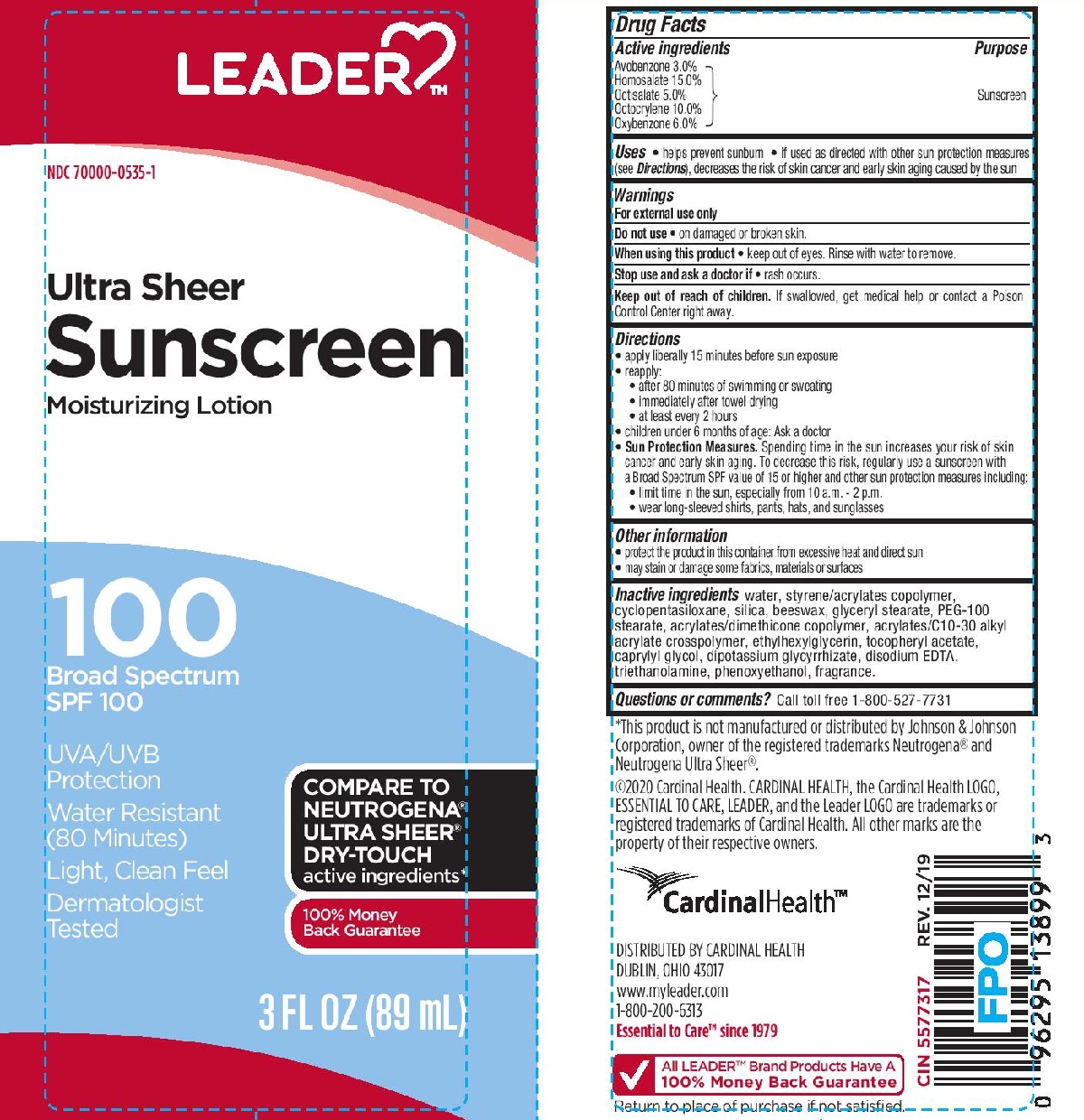 DRUG LABEL: Leader
NDC: 70000-0535 | Form: LOTION
Manufacturer: CARDINAL HEALTH, INC.
Category: otc | Type: HUMAN OTC DRUG LABEL
Date: 20251202

ACTIVE INGREDIENTS: AVOBENZONE 30 mg/1 mL; HOMOSALATE 150 mg/1 mL; OCTISALATE 50 mg/1 mL; OCTOCRYLENE 100 mg/1 mL; OXYBENZONE 60 mg/1 mL
INACTIVE INGREDIENTS: DIMETHICONE; GLYCERYL STEARATE/PEG-100 STEARATE; SILICON DIOXIDE; BUTYL METHACRYLATE/METHYL METHACRYLATE/METHACRYLIC ACID/STYRENE CROSSPOLYMER; CARBOMER COPOLYMER TYPE A; ALPHA-TOCOPHEROL ACETATE; EDETATE DISODIUM; WATER; ETHYLHEXYLGLYCERIN; CAPRYLYL GLYCOL; GLYCYRRHIZINATE DIPOTASSIUM; TROLAMINE; WHITE WAX; CYCLOMETHICONE 5; PHENOXYETHANOL

Leader Ultra Sheer SPF 100 Sunscreen Lotion

Active ingredients

Avobenzone 3.0%, Homosalate 15.0%, Octisalate 5.0%, Octocrylene 10.0%, Oxybenzone 6.0%

Purpose

Sunscreen

Uses

- helps prevent sunburn
- if used as directed with other sun protection measures (see Directions), decreases the risk of skin cancer and early skin aging caused by the sun

Warnings

For external use only

Do not use

• on damaged or broken skin.

When using this product

• keep out of eyes. Rinse with water to remove.

Stop use and ask a doctor if

• rash occurs.

Keep out of reach of children.

If swallowed, get medical help or contact a Poison Control Center right away.

Directions

• apply liberally 15 minutes before sun exposure

reapply:
• after 80 minutes of swimming or sweating
• immediately after towel drying
• at least every 2 hours
• children under 6 months of age: Ask a doctor
Sun Protection Measures. Spending time in the sun increases your risk of skin cancer and early skin aging. To decrease this risk, regularly use a sunscreen with a Broad Spectrum SPF value of 15 or higher and other sun protection measures including:
• limit time in the sun, especially from 10 a.m. - 2 p.m.
• wear long-sleeved shirts, pants, hats, and sunglasses

Other information

• protect this product in this container from excessive heat and direct sun
• may stain or damage some fabrics, materials or surfaces

Inactive ingredients

water, styrene/acylates copolymer, cyclopentasiloxane, silica, beeswax, glyceryl stearate, PEG-100 stearate, acrylates/dimethicone copolymer, acrylates/C10-30 alkyl acrylate crosspolymer, ethylhexylglycerin, tocopheryl, caprylyl glycol, dipotassium glycyrrhizate, disodium EDTA, triethanolamine, phenoxyethanol, fragrance.

Label

Leader Ultra Sheer SPF 100 Sunscreen Lotion

3 FL OZ (89 mL)

NDC 70000-0535-1